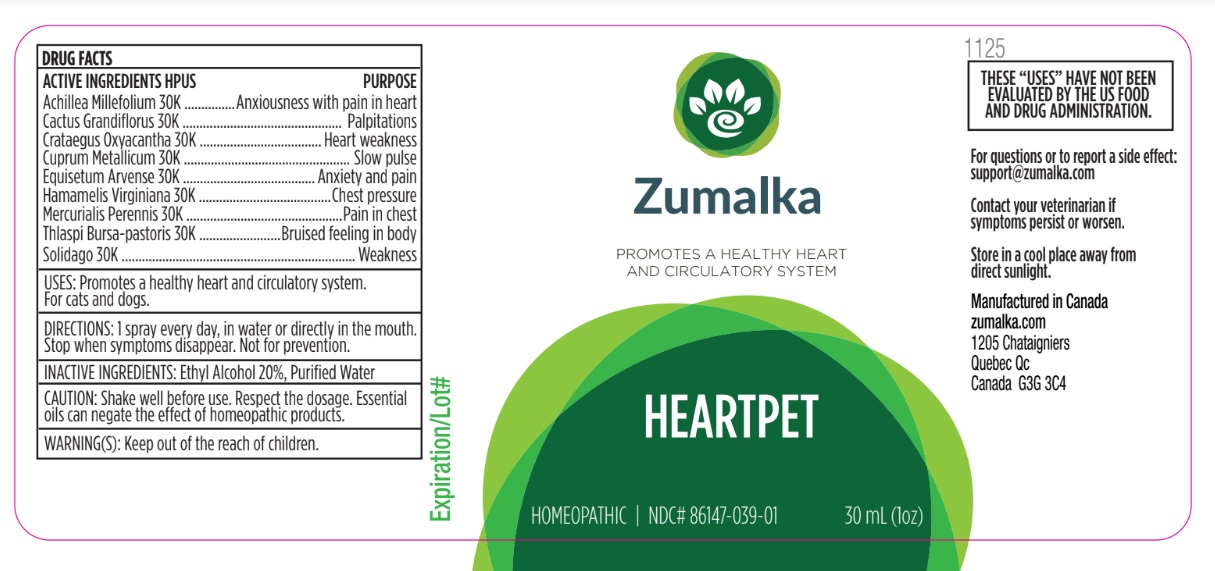 DRUG LABEL: HEARTPET
NDC: 86147-039 | Form: LIQUID
Manufacturer: Groupe Cyrenne Inc.
Category: homeopathic | Type: OTC ANIMAL DRUG LABEL
Date: 20251120

ACTIVE INGREDIENTS: ACHILLEA MILLEFOLIUM WHOLE 30 [kp_C]/30 mL; SELENICEREUS GRANDIFLORUS STEM 30 [kp_C]/30 mL; CRATAEGUS LAEVIGATA FLOWER 30 [kp_C]/30 mL; COPPER 30 [kp_C]/30 mL; EQUISETUM ARVENSE TOP 30 [kp_C]/30 mL; HAMAMELIS VIRGINIANA ROOT BARK/STEM BARK 30 [kp_C]/30 mL; MERCURIALIS PERENNIS WHOLE 30 [kp_C]/30 mL; CAPSELLA BURSA-PASTORIS WHOLE 30 [kp_C]/30 mL; SOLIDAGO VIRGAUREA FLOWERING TOP 30 [kp_C]/30 mL
INACTIVE INGREDIENTS: ALCOHOL; WATER

Active ingredients Purpose

Achillea Millefolium 30k Anxiousness with pain in heart

Cactus Grandiflorus 30k Palpitations

Crataegus Oxyacantha 30k Heart weakness

Cuprum Metallicum 30k Slow pulse

Equisetum Arvense 30k Anxiety and pain

Hamamelis Virginiana 30k Chest pressure

Mercurialis Perennis 30k Pain in chest

Thlaspi Bursa-pastoris 30k Bruised feeling in body

Solidago 30k Weakness

Uses

Promotes a healthy heart and circulatory system. For cats and dogs

Warnings

Keep out of reach of children.

Direction

1 spray every day, in water or directly in the mouth. Stop when symptoms disappear. Not for prevention.

Inactive ingredients

Ethyl alcohol 20%, purified water

Cautions

Shake well before use. Respect the dosage. Essential oils can negate the effects of homeopathic products. Store in a cool place away from direct sunlight.